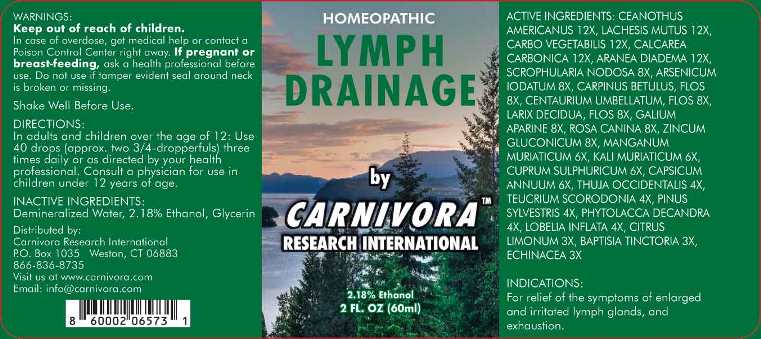 DRUG LABEL: Lymph Drainage
NDC: 69134-0002 | Form: LIQUID
Manufacturer: Carnivora Research International
Category: homeopathic | Type: HUMAN OTC DRUG LABEL
Date: 20220906

ACTIVE INGREDIENTS: BAPTISIA TINCTORIA WHOLE 3 [hp_X]/1 mL; LEMON JUICE 3 [hp_X]/1 mL; ECHINACEA ANGUSTIFOLIA WHOLE 3 [hp_X]/1 mL; LOBELIA INFLATA WHOLE 4 [hp_X]/1 mL; PHYTOLACCA AMERICANA ROOT 4 [hp_X]/1 mL; PINUS SYLVESTRIS LEAFY TWIG 4 [hp_X]/1 mL; TEUCRIUM SCORODONIA FLOWERING TOP 4 [hp_X]/1 mL; THUJA OCCIDENTALIS LEAFY TWIG 4 [hp_X]/1 mL; CAPSICUM 6 [hp_X]/1 mL; CUPRIC SULFATE 6 [hp_X]/1 mL; POTASSIUM CHLORIDE 6 [hp_X]/1 mL; MANGANESE CHLORIDE 6 [hp_X]/1 mL; ARSENIC TRIIODIDE 8 [hp_X]/1 mL; CARPINUS BETULUS FLOWERING TOP 8 [hp_X]/1 mL; CENTAURIUM ERYTHRAEA FLOWER 8 [hp_X]/1 mL; GALIUM APARINE WHOLE 8 [hp_X]/1 mL; LARIX DECIDUA FLOWERING TOP 8 [hp_X]/1 mL; ROSA CANINA FRUIT 8 [hp_X]/1 mL; SCROPHULARIA NODOSA WHOLE 8 [hp_X]/1 mL; ZINC GLUCONATE 8 [hp_X]/1 mL; ARANEUS DIADEMATUS 12 [hp_X]/1 mL; OYSTER SHELL CALCIUM CARBONATE, CRUDE 12 [hp_X]/1 mL; ACTIVATED CHARCOAL 12 [hp_X]/1 mL; CEANOTHUS AMERICANUS LEAF 12 [hp_X]/1 mL; LACHESIS MUTA VENOM 12 [hp_X]/1 mL
INACTIVE INGREDIENTS: WATER; GLYCERIN; ALCOHOL

DRUG FACTS:

ACTIVE INGREDIENTS:

Ceanothus Americanus 12X, Lachesis Mutus 12X, Carbo Vegetabilis 12X, Calcarea Carbonica 12X, Aranea Diadema 12X, Scrophularia Nodosa 8X, Arsenicum Iodatum 8X, Carpinus Betulus, Flos 8X, Centaurium Umbellatum, Flos 8X, Larix Decidua, Flos 8X, Galium Aparine 8X, Rosa Canina 8X, Zincum Gluconicum 8X, Manganum Muriaticum 6X, Kali Muriaticum 6X, Cuprum Sulphuricum 6X, Capsicum Annuum 6X, Thuja Occidentalis 4X, Teucrium Scorodonia 4X, Pinus Sylvestris 4X, Phytolacca Decandra 4X, Lobelia Inflata 4X, Citrus Limonum 3X, Baptisia Tinctoria 3X, Echinacea (Angustifolia) 3X.

INDICATIONS:

For relief of symptoms of enlarged and irritated lymph glands, and exhaustion.

WARNINGS:

Keep out of reach of children. In case of overdose, get medical help or contact a Poison Control Center right away.

If pregnant or breast-feeding, ask a health professional before use. Do not use if tamper evident seal around neck is broken or missing.

Shake Well Before Use.

Keep out of reach of children. In case of overdose, get medical help or contact a Poison Control Center right away.

DIRECTIONS:

In adults and children over the age of 12: Use 40 drops (approx. two 3/4-dropperfuls) three times daily or as directed by your health professional. Consult a physician for use in children under 12 years of age.

INDICATIONS:

For relief of symptoms of enlarged and irritated lymph glands, and exhaustion.

INACTIVE INGREDIENTS:

Demineralized Water, 2.18% Ethanol, Glycerin

QUESTIONS:

Distributed by:

Carnivora Research International

P.O. Box 1035 Weston, Ct 06883

866-836-8735

Visit us at www.carnivora.com

Email: info@carnivora.com

PACKAGE LABEL DISPLAY

HOMEOPATHIC

LYMPH

DRAINAGE

by

CARNIVORA

RESEARCH INTERNATIONAL

2 FL. OZ (60ml)